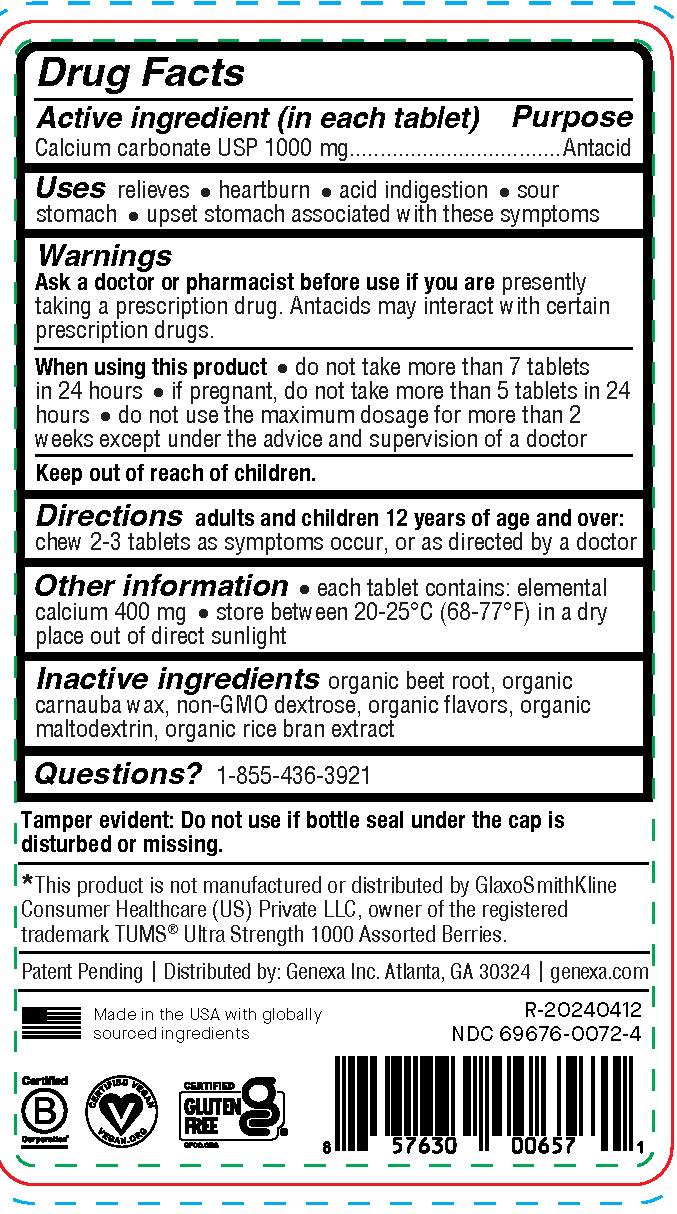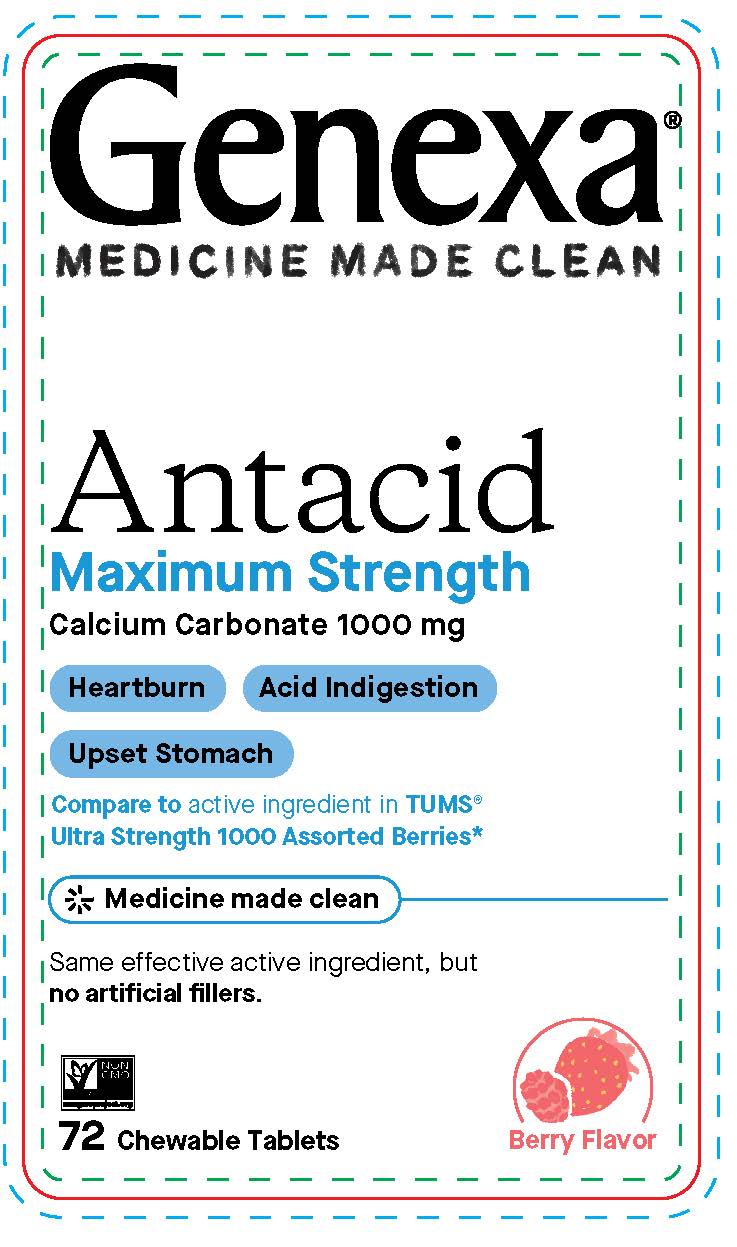 DRUG LABEL: Genexa Antacid
NDC: 69676-0072 | Form: TABLET, CHEWABLE
Manufacturer: Genexa Inc.
Category: otc | Type: HUMAN OTC DRUG LABEL
Date: 20250207

ACTIVE INGREDIENTS: CALCIUM CARBONATE 1000 mg/1 1
INACTIVE INGREDIENTS: BEET; CARNAUBA WAX; DEXTROSE; MALTODEXTRIN; RICE BRAN

Antacid Maximum Strength

Drug Facts

Active ingredient (in each tablet)

Calcium carbonate USP 1000 mg

Purpose

Antacid

INDICATIONS AND USAGE

Uses relieves

- heartburn
- acid indigestion
- sour stomach
- upset stomach associated with these symptoms

Warnings

Ask a doctor or pharmacist before use if you are presently taking a prescription drug. Antacids may interact with certain prescription drugs.

When using this product

- do not take more than 7 tablets in 24 hours
- if pregnant, do not take more than 5 tablets in 24 hours
- do not use the maximum dosage for more than 2 weeks except under the advice and supervision of a doctor

Keep out of reach of children

Directions

adults and children 12 years of age and over: chew 2-3 tablets as symptoms occur, or as directed by a doctor

Other information

- each tablet contains: elemental calcium 400 mg
- store between 20-25°C (68-77°F) in a dry place out of direct sunlight

INACTIVE INGREDIENT

Inactive ingredients organic beet root, organic carnauba wax, non-GMO dextrose, organic flavors, organic maltodextrin, organic rice bran extract

Questions?1-855-436-3921

Tamper evident: Do not use if bottle seal under the cap is disturbed or missing.

*This product is not manufactured or distributed by GlaxoSmithKline Consumer Healthcare (US) Private LLC, owner of the registered trademark TUMS® Ultra Strength 1000 Assorted Berries.

Patent Pending | Distributed by: Genexa Inc., Atlanta, GA 30324 | genexa.com

Made in the USA with globally sourced ingredients

NDC 69676-0072-4

PACKAGE LABEL

Genexa®

MEDICINE MADE CLEAN

Antacid Maximum Strength

Calcium Carbonate 1000 mg

Heartburn

Acid Indigestion

Upset Stomach

Compare to active ingredient in TUMS® Ultra Strength 1000 Assorted Berries*

Medicine made clean

Same effective active ingredient, but no artificial fillers.

Organic Berry & Vanilla Flavor

72 Chewable Tablets